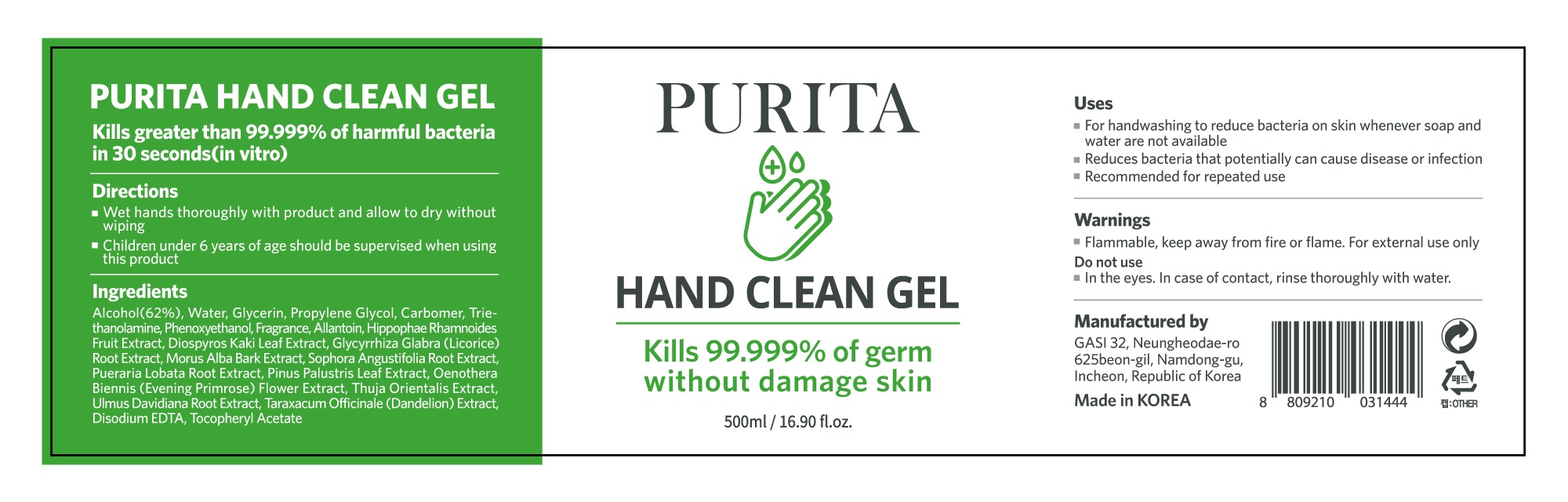 DRUG LABEL: PURITA HAND CLEAN gel
NDC: 77174-0001 | Form: GEL
Manufacturer: GASI CO LTD
Category: otc | Type: HUMAN OTC DRUG LABEL
Date: 20200501

ACTIVE INGREDIENTS: ALCOHOL 62 mL/100 mL
INACTIVE INGREDIENTS: TROLAMINE; WATER; ALLANTOIN; CARBOMER 940; GLYCERIN

Drug Facts

ACTIVE INGREDIENT

alcohol

PURPOSE

sterilization of hands, skin and so on

KEEP OUT OF REACH OF THE CHILDREN

INDICATIONS AND USAGE

take appropriate amount on the hand, rub and dry well

WARNINGS

■ Flammable. Keep away from fire or flame.

■ For external use only.

■ Do not use in eyes.

■ lf swallowed, get medical help promptly.

■ Stop use, ask doctor lf irritation occurs.

■ Keep out of reach of children.

DOSAGE AND ADMINISTRATION

for external use only

INACTIVE INGREDIENT

water, glycerin, propylene glycol, carbomer etc.